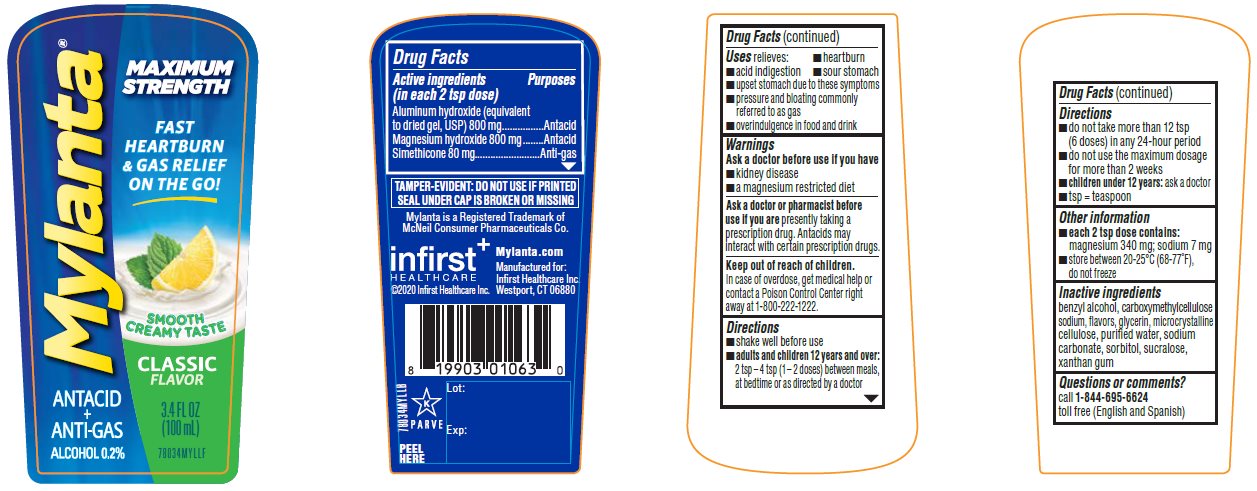 DRUG LABEL: Mylanta Maximum Strength Classic Flavor
NDC: 62372-500 | Form: SUSPENSION
Manufacturer: Infirst Healthcare Inc.
Category: otc | Type: HUMAN OTC DRUG LABEL
Date: 20230201

ACTIVE INGREDIENTS: ALUMINUM HYDROXIDE 800 mg/10 mL; MAGNESIUM HYDROXIDE 800 mg/10 mL; DIMETHICONE 80 mg/10 mL
INACTIVE INGREDIENTS: BENZYL ALCOHOL; CARBOXYMETHYLCELLULOSE SODIUM, UNSPECIFIED; GLYCERIN; MICROCRYSTALLINE CELLULOSE; WATER; SODIUM CARBONATE; SORBITOL; SUCRALOSE; XANTHAN GUM

Mylanta Maximum Strength Classic Flavor 3.4 FL OZ

Active ingredients (in each 2 tsp dose)

Aluminum hydroxide
(equivalent to dried gel, USP) 800 mg

Magnesium hydroxide 800 mg

Simethicone 80 mg

Purpose

Antacid

Antacid

Anti-gas

Uses

relieves:

- heartburn
- acid indigestion
- sour stomach
- upset stomach due to these symptoms
- pressure and bloating commonly referred to as gas
- overindulgence in food and drink

Warnings

Ask a doctor before use if you have

- kidney disease
- a magnesium restricted diet

Ask a doctor or pharmacist before use if you are

presently taking a prescription drug. Antacids may interact with certain prescription drugs.

Keep out of reach of children.

In case of overdose, get medical help or contact a Poison Control Center right away at 1-800-222-1222.

Directions

- shake well before use
- adults and children 12 years and over:
  2 tsp – 4 tsp (1-2 doses) between meals, at bedtime or as directed by a doctor
- do not take more than 12 tsp (6 doses) in any 24-hour period
- do not use the maximum dosage for more than 2 weeks
- children under 12 years: ask a doctor
- tsp = teaspoon

Other information

- each 2 tsp dose contains: magnesium 340 mg; sodium 7 mg
- store between 20-25°C (68-77°F), do not freeze

Inactive ingredients

benzyl alcohol, carboxymethylcellulose sodium, flavors, glycerin, microcrystalline cellulose, purified water, sodium carbonate, sorbitol, sucralose, xanthan gum

Questions or comment?

call 1-844-695-6624 toll free (English and Spanish)

Principal Display Panel

MYLANTA®
ANTACID
+
ANTI-GAS
Alcohol 0.2%

MAXIMUM STRENGTH

FAST HEARTBURN & GAS RELIEF ON THE GO!

SMOOTH CREAMY TASTE

CLASSIC
FLAVOUR

3.4 FL OZ (100 mL)

78034MYLLF

TAMPER-EVIDENT: DO NOT USE IF PRINTED SEAL UNDER CAP IS BROKEN OR MISSING

Mylanta is a Registered Trademark of McNeil Consumer Pharmaceuticals Co.

infirst^+
HEALTHCARE
©2020 Infirst Healthcare Inc.

Mylanta.com

Manufactured for:
Infirst Healthcare Inc.
Westport, CT 06880